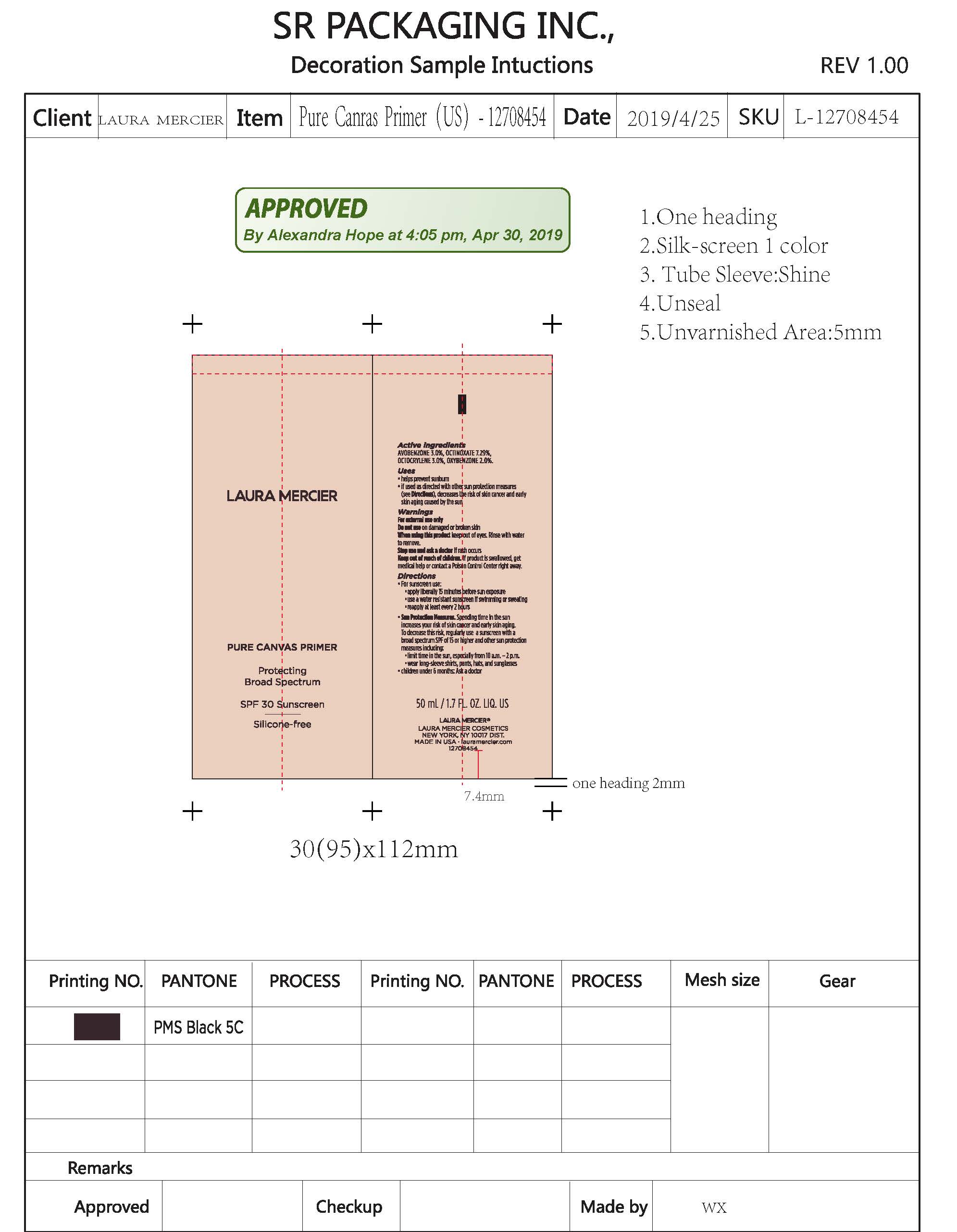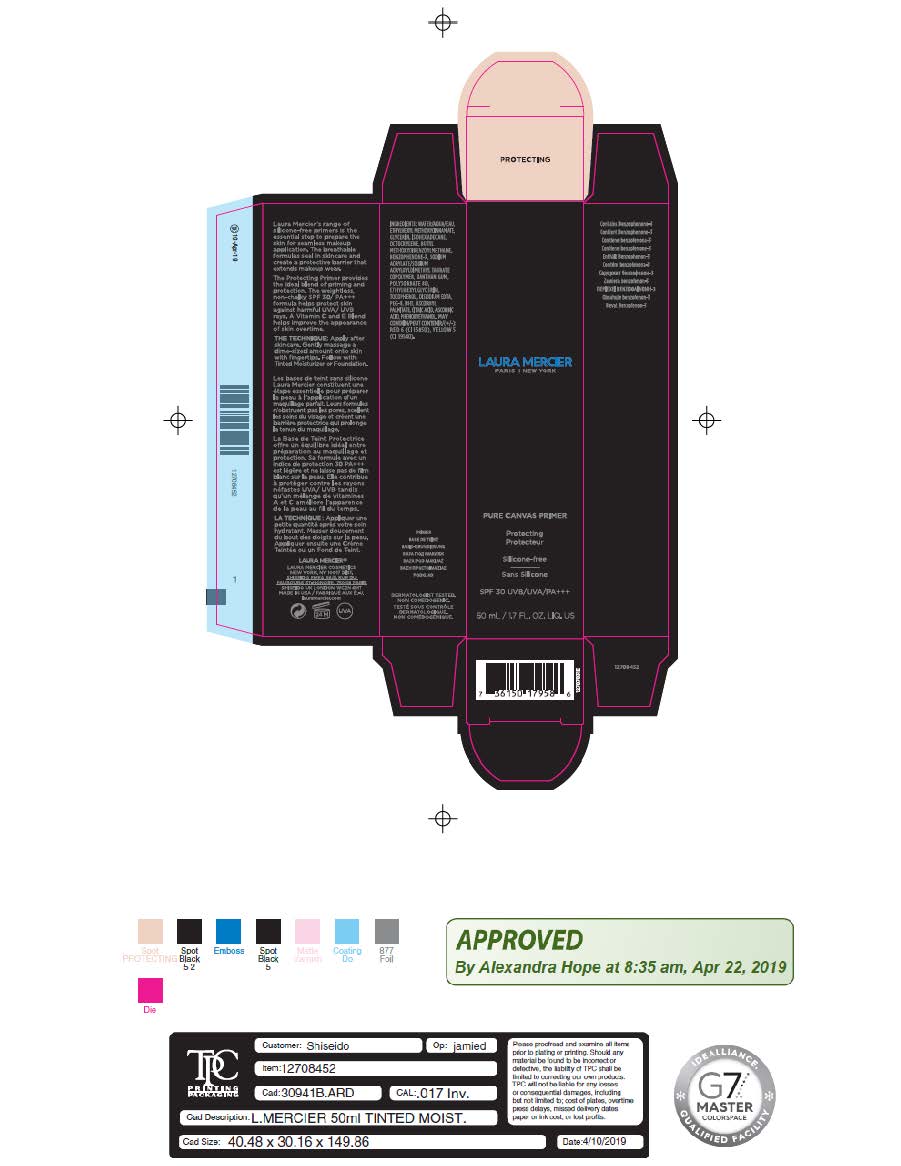 DRUG LABEL: Moisturizer
NDC: 61354-039 | Form: CREAM
Manufacturer: Oxygen Development LLC
Category: otc | Type: HUMAN OTC DRUG LABEL
Date: 20220103

ACTIVE INGREDIENTS: AVOBENZONE 3 g/100 g; OCTOCRYLENE 3 g/100 g; OXYBENZONE 2 g/100 g; OCTINOXATE 7.29 g/100 g
INACTIVE INGREDIENTS: GLYCERIN 4.98 g/100 g; XANTHAN GUM 0.2 g/100 g; WATER 72.61 g/100 g; ISOHEXADECANE 4.56 g/100 g; PHENOXYETHANOL 0.9 g/100 g; SODIUM ACRYLATE/SODIUM ACRYLOYLDIMETHYLTAURATE COPOLYMER (4000000 MW) 0.93 g/100 g

Laura Mercier Pure Canvas Primer Protecting Broad Spectrum Spf 30 Sunscreen

Active ingredients

Avobenzone 3.0%, Octinoxate 7.29%, Octocrylene 3.0%, Oxybenzone 2.0%

Uses

Helps prevent sunburn

If used as directed with other sun protections measures (see Directions), decreases the risk of skin cancer and early skin again caused by the sun

Warnings

For external use only

Do not use on damage or broken skin

When using

When using this product keep out of eyes. Rinse with water to remove.

Stop use

Stop use and ask a doctor if rash occurs

Keep out of reach of children. If product is swallowed, get medical help or contact a Poison Control Center right away.

Directions

For sunscree use: apply liberally 15 minutes sun exposure. Use a water resistant sunscreen if swimming or sweating. reapply at least every 2 hours.

Sun protections measures. Spending time in the sun increases your risk of skin cancer and early skin again. To decrease this risk, regulary use a sunscreen with a broad spectrum SPF of 15 or higher and other sun protection measures including: lomit time in the sun, especially from 10 a.m - 2 p.m. wear long - sleeve shirts, pants, hats, and sunglasses. Children unther 6 months: ask a doctor.

Other information

Protect the product in this container from excessive heat and direct sun